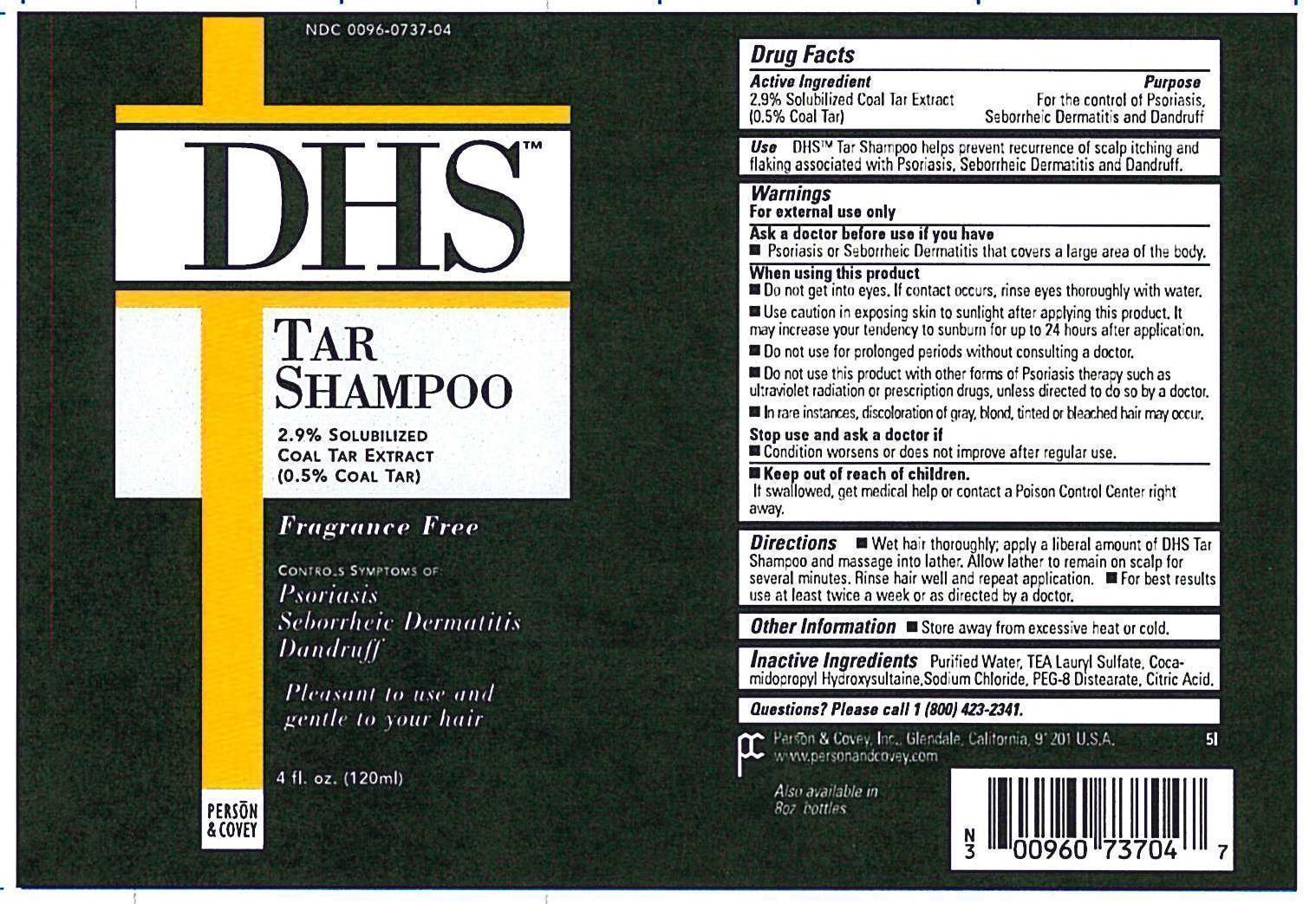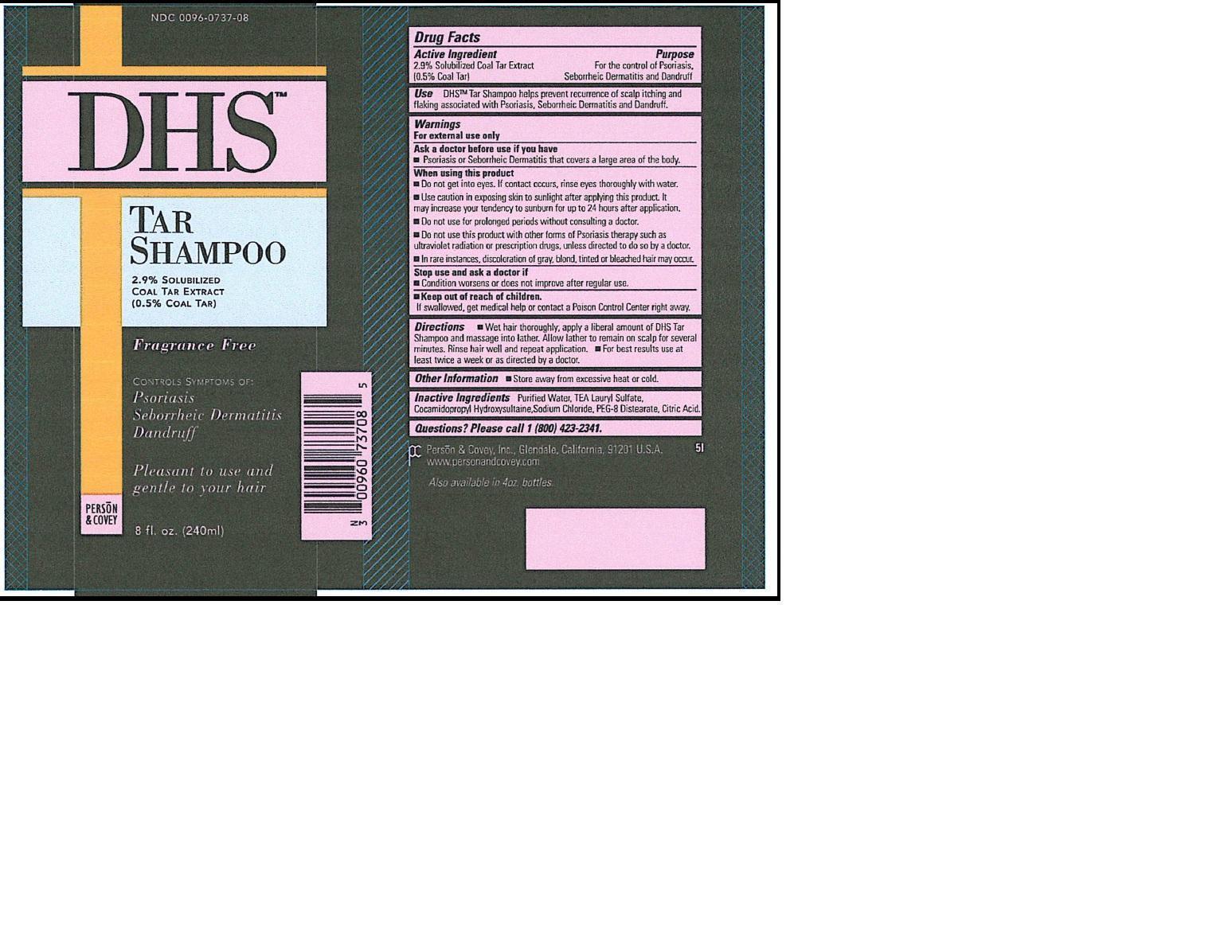 DRUG LABEL: DHS TAR
NDC: 0096-0737 | Form: SHAMPOO
Manufacturer: Person and Covey
Category: otc | Type: HUMAN OTC DRUG LABEL
Date: 20251128

ACTIVE INGREDIENTS: COAL TAR 0.005 g/1 g
INACTIVE INGREDIENTS: TRIETHANOLAMINE LAURYL SULFATE; COCAMIDOPROPYL HYDROXYSULTAINE; PEG-8 DISTEARATE; SODIUM CHLORIDE; ANHYDROUS CITRIC ACID; WATER

DHS TAR

WARNINGS

For external use only. Ask a physician before use if you have Psoriasis or Seborrheic Dermatitis that covers a large area of the body. Do not get into eyes. If contact occurs, rinse eyes thoroughly with water. Use caution in exposing skin to sunlight after applying this product. It may increase your tendency to sunburn for up to 24 hours after application. Do not use for prolonged periods without consulting a physician. Do not use this product with other forms of Psoriasis therapy such as ultraviolet radiation or prescription drugs, unless directed to do so by a physician. In rare instances, discoloration of gray, blond tinted or bleached hair may occur. Stop use and ask physician if condition worsens or does not improve after regular use. Store away from excessive heat or cold.

Dosage and Administration

Wet hair thoroughly, apply a liberal amount of shampoo and massage into lather. Allow lather to remain on scalp for several minutes. Rinse hair well and repeat application. For best results use at least twice a week or as directed by a physician.

Indications and Use

Helps prevent recurrence of scalp itching and flaking associated with Psoriasis, Seborrheic Dermatitis and Dandruff.

Keep out of the Reach of Children

Yes. If swallowed, get medical help or contact a Poison Control Center right away.

Purpose

Controls symptoms of Psoriasis, Seborrheic Dermatitis and Dandruff.

Inactive Ingredients

Purified Water

Triethanolamine Lauryl Sulfate

Cocamidopropyl Hydroxysultaine

PEG 8 Distearate

Sodium Chloride

Hydroxypropyl Methylcellulose

Lemon fruit oil

Citric Acid

Active Ingredient

Coal Tar

PACKAGE LABEL.PRINCIPAL DISPLAY

dhs tar shampoo 4 oz.jpg

PACKAGE LABEL.PRINCIPAL DISPLAY

dhs tar shampoo 8 oz.jpg